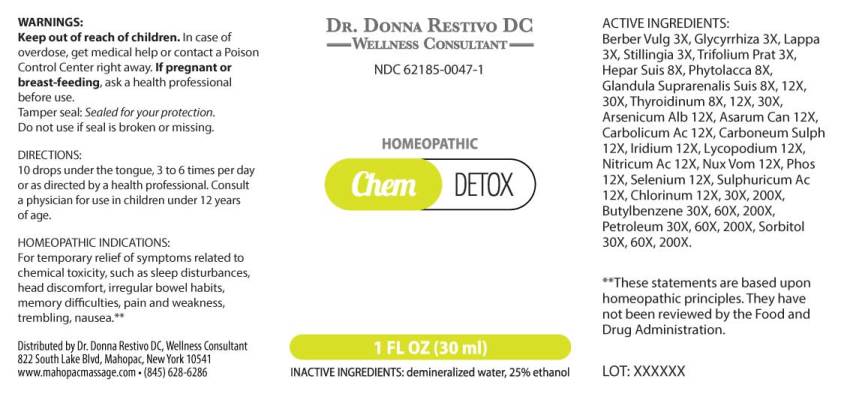 DRUG LABEL: ChemDetox
NDC: 62185-0047 | Form: LIQUID
Manufacturer: Dr. Donna Restivo DC
Category: homeopathic | Type: HUMAN OTC DRUG LABEL
Date: 20230110

ACTIVE INGREDIENTS: BERBERIS VULGARIS ROOT BARK 3 [hp_X]/1 mL; GLYCYRRHIZA GLABRA 3 [hp_X]/1 mL; ARCTIUM LAPPA ROOT 3 [hp_X]/1 mL; STILLINGIA SYLVATICA ROOT 3 [hp_X]/1 mL; TRIFOLIUM PRATENSE FLOWER 3 [hp_X]/1 mL; SUS SCROFA ADRENAL GLAND 8 [hp_X]/1 mL; PORK LIVER 8 [hp_X]/1 mL; PHYTOLACCA AMERICANA ROOT 8 [hp_X]/1 mL; SUS SCROFA THYROID 8 [hp_X]/1 mL; ARSENIC TRIOXIDE 12 [hp_X]/1 mL; ASARUM CANADENSE ROOT 12 [hp_X]/1 mL; PHENOL 12 [hp_X]/1 mL; CARBON DISULFIDE 12 [hp_X]/1 mL; IRIDIUM 12 [hp_X]/1 mL; LYCOPODIUM CLAVATUM SPORE 12 [hp_X]/1 mL; NITRIC ACID 12 [hp_X]/1 mL; STRYCHNOS NUX-VOMICA SEED 12 [hp_X]/1 mL; PHOSPHORUS 12 [hp_X]/1 mL; SELENIUM 12 [hp_X]/1 mL; SULFURIC ACID 12 [hp_X]/1 mL; CHLORINE 30 [hp_X]/1 mL; BUTYLBENZENE 30 [hp_X]/1 mL; KEROSENE 30 [hp_X]/1 mL; SORBITOL 30 [hp_X]/1 mL
INACTIVE INGREDIENTS: WATER; ALCOHOL

Drug Facts:

ACTIVE INGREDIENTS:

Berberis Vulgaris 3X, Glycyrrhiza Glabra 3X, Lappa Major 3X, Stillingia Sylvatica 3X, Trifolium Pratense 3X, Hepar Suis 8X, Phytolacca Decandra 8X, Glandula Suprarenalis Suis 8X, Thyroidinum (Suis) 8X, Arsenicum Album 12X, Asarum Canadense 12X, Carbolicum Acidum 12X, Carboneum Sulphuratum 12X, Iridium Metallicum 12X, Lycopodium Clavatum 12X, Nitricum Acidum 12X, Nux Vomica 12X, Phosphorus 12X, Selenium Metallicum 12X, Sulphuricum Acidum 12X, Chlorinum 12X, 30X, 200X, Butylbenzene 30X, 60X, 200X, Petroleum 30X, 60X, 200X, Sorbitol 30X, 60X, 200X.

HOMEOPATHIC INDICATIONS:

For temporary relief of symptoms related to chemical toxicity such as sleep disturbances, head discomfort, irregular bowel habits, memory difficulties, pain and weakness, trembling, nausea.**

**These statements are based upon homeopathic principles. They have not been reviewed by the Food and Drug Administration.

WARNINGS:

Keep out of reach of children. In case of overdose, get medical help or contact a Poison Control Center right away.

If pregnant or breast-feeding, ask a health professional before use.

Tamper seal: Sealed for your protection.

Do not use if seal is broken or missing.

Keep out of reach of children. In case of overdose, get medical help or contact a Poison Control Center right away.

DIRECTIONS:

10 drops under the tongue, 3 to 6 times a day or as directed by a health professional. Consult a physician for use in children under 12 years of age.

HOMEOPATHIC INDICATIONS:

For temporary relief of symptoms related to chemical toxicity such as sleep disturbances, head discomfort, irregular bowel habits, memory difficulties, pain and weakness, trembling, nausea.**

**These statements are based upon homeopathic principles. They have not been reviewed by the Food and Drug Administration.

INACTIVE INGREDIENTS:

demineralized water, 25% ethanol

QUESTIONS:

Distributed by Dr. Donna Restivo DC, Wellness Consultant

822 South Lake Blvd. Mahopac, New York 10541

www.mahopacmassage.com • (845) 628-6286

PACKAGE LABEL DISPLAY:

DR. DONNA RESTIVO DC

WELLNESS CONSULTANT

NDC 62185-0047-1

HOMEOPATHIC

ChemDETOX

1 FL OZ (30 ml)